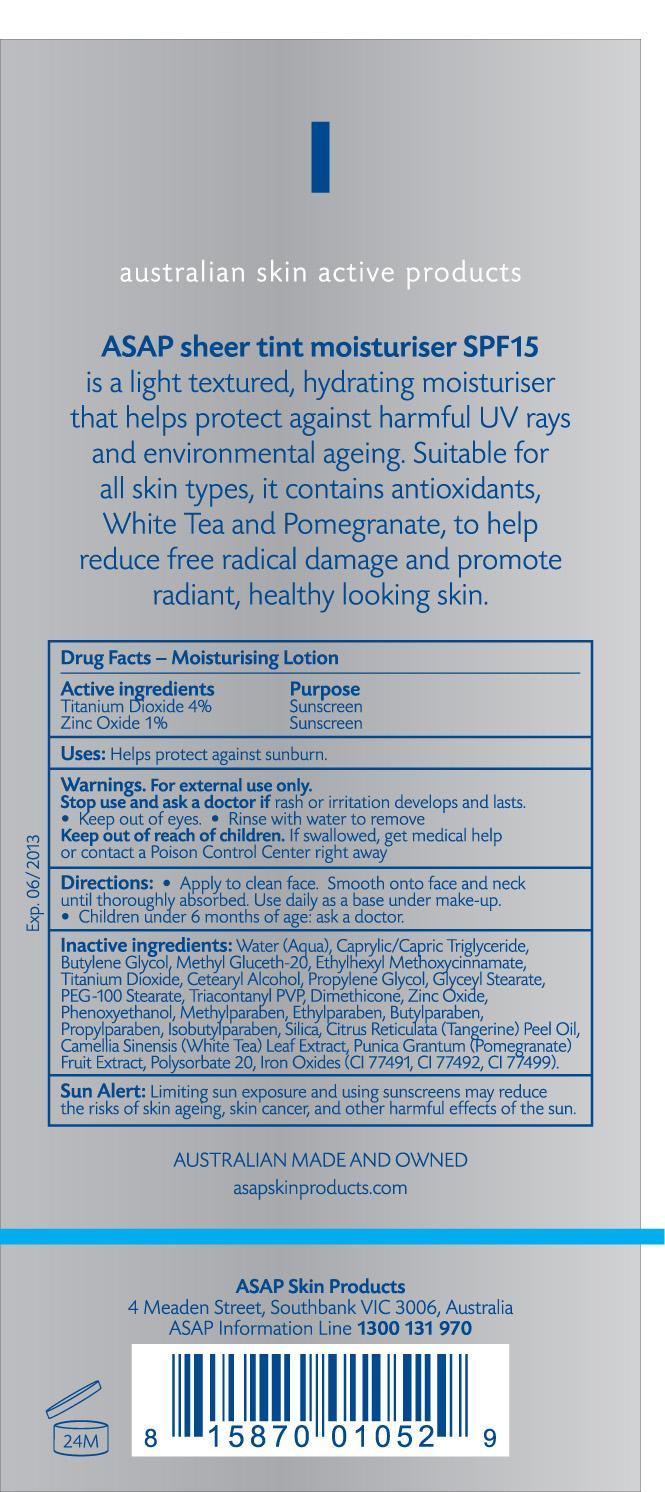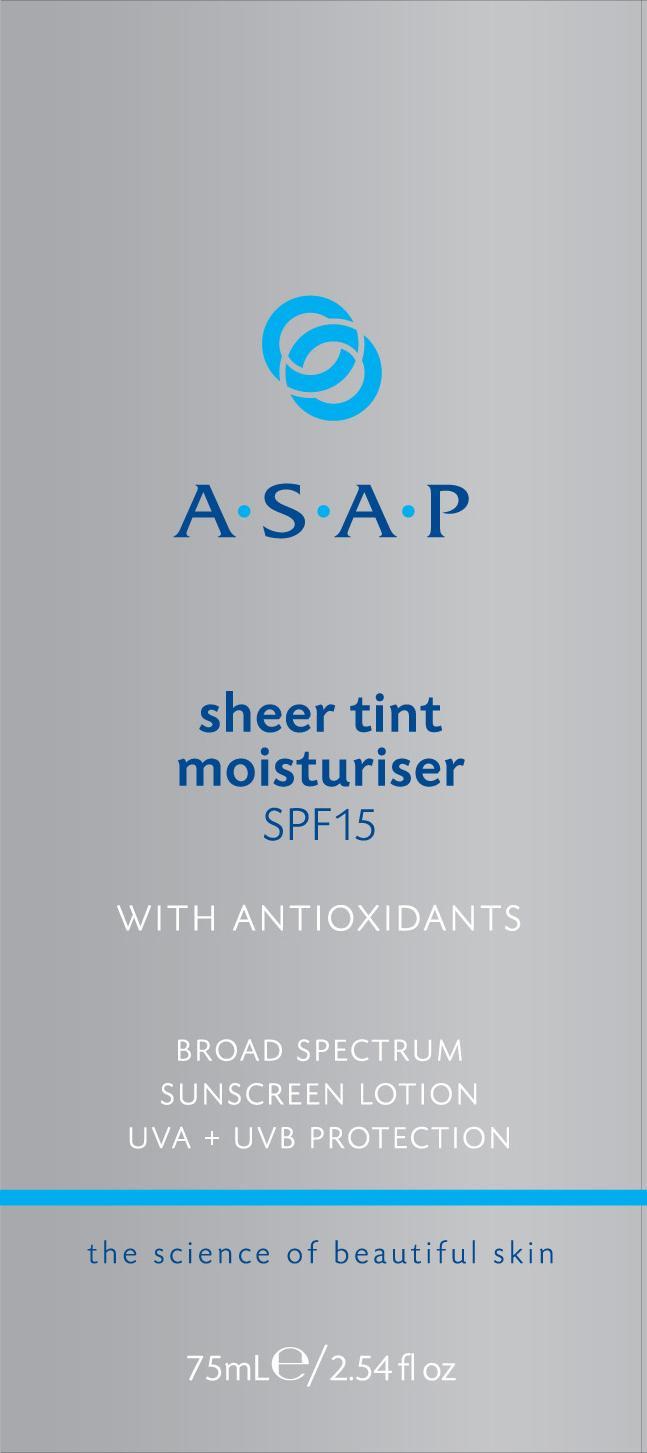 DRUG LABEL: Sheer Tint Moisturizer SPF 15
NDC: 76261-250 | Form: LOTION
Manufacturer: AUSTRALIAN SKIN PRODUCTS PTY LTD
Category: otc | Type: HUMAN OTC DRUG LABEL
Date: 20130208

ACTIVE INGREDIENTS: TITANIUM DIOXIDE 4 g/100 mL; ZINC OXIDE 1 g/100 mL
INACTIVE INGREDIENTS: WATER; BUTYLENE GLYCOL; METHYL GLUCETH-20; OCTINOXATE; CETOSTEARYL ALCOHOL; PROPYLENE GLYCOL; GLYCERYL MONOSTEARATE; PEG-100 STEARATE; DIMETHICONE; ZINC OXIDE; PHENOXYETHANOL; METHYLPARABEN; ETHYLPARABEN; BUTYLPARABEN; PROPYLPARABEN; ISOBUTYLPARABEN; SILICON DIOXIDE; CITRUS RETICULATA FRUIT OIL; BANCHA TEA LEAF/TWIG; POMEGRANATE; POLYSORBATE 20; FERRIC OXIDE RED; FERRIC OXIDE YELLOW; FERROSOFERRIC OXIDE

Sheer Tint Moisturizer SPF 15

Active Ingredients Purpose
Titanium Dioxide 4% Sunscreen
Zinc Oxide 1% Sunscreen

PURPOSE

Uses: Help protect against sunburn

Keep out of reach of children

Stop use and ask a doctor if rash or irritation develops and lasts. Keep out of eyes.

WARNINGS

For external use only.
Rinse with water to remove.
If swallowed, get medical help or contact a poison control center right away.

Directions
Apply to clean face. smooth onto face and neck until thoroughly absorbed. Use daily as a base under make up.
Children under 6 months of age: ask a doctor.

INACTIVE INGREDIENT

Inactive Ingredients: Water (Aqua), Caprylic/capric triglyceride, butylene glycol, Methyl Gluceth-20, Ethylhexyl methoxycinnamate, Titanium Dioxide, Cetearyl Alcohol, Propylene glycol, glyceryl stearate, PEG-100 stearate, triacontanyl PVP, dimethicone, zinc oxide, phenoxyethanol, methylparaben, ethylparaben, butylparaben, propylparaben, Isobutylparaben, silica, citrus reticulata (tangerine) peel oil, camellia sinensis (white tea) leaf extract, punica granatum (pomegranate) fruit extract, polysorbate 20, Iron oxides (CI 77491, CI77492, CI77499).

PACKAGE LABEL

Sheer tint moisturizer SPF 15
With antioxidants

broad spectrum
Sunscreen lotion
UVA+UVB protection

75 mL/2.54fl oz